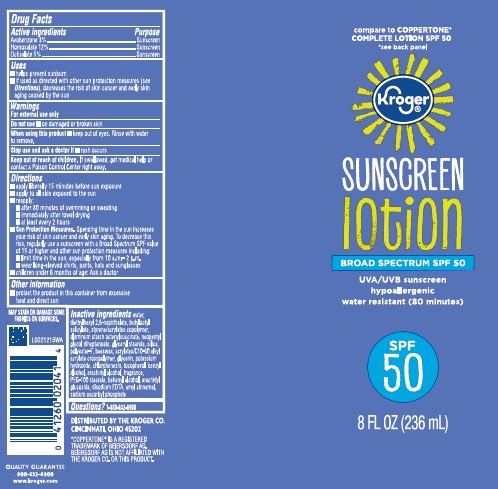 DRUG LABEL: Moisturizing Sunscreen SPF 50
NDC: 59450-954 | Form: LOTION
Manufacturer: The Kroger Co.
Category: otc | Type: HUMAN OTC DRUG LABEL
Date: 20260227

ACTIVE INGREDIENTS: AVOBENZONE 30 mg/1 mL; HOMOSALATE 120 mg/1 mL; OCTISALATE 50 mg/1 mL
INACTIVE INGREDIENTS: WATER; DIETHYLHEXYL 2,6-NAPHTHALATE; BUTYLOCTYL SALICYLATE; STYRENE/ACRYLAMIDE COPOLYMER (500000 MW); ALUMINUM STARCH OCTENYLSUCCINATE; NEOPENTYL GLYCOL DIHEPTANOATE; GLYCERYL MONOSTEARATE; SILICON DIOXIDE; POLYESTER-7; YELLOW WAX; CARBOMER COPOLYMER TYPE A (ALLYL PENTAERYTHRITOL CROSSLINKED); GLYCERIN; POTASSIUM HYDROXIDE; CHLORPHENESIN; TOCOPHEROL; BENZYL ALCOHOL; ARACHIDYL ALCOHOL; PEG-100 STEARATE; DOCOSANOL; ARACHIDYL GLUCOSIDE; EDETATE DISODIUM ANHYDROUS; .ALPHA.-AMYLCINNAMALDEHYDE; SODIUM ASCORBYL PHOSPHATE

Kroger D54.000/D54AA
Moisturizing Sunscreen Lotion SPF 50

Active ingredients

Avobenzone 3%

Homosalate 12%

Octisalate 5%

Purpose

Sunscreen

Uses

- helps prevent sunburn
- if used as directed with other sun protections measures (see Directions), decreases the risk of skin cancer and early skin aging caused by the sun

Warnings

For external use only

Do not use

- on damaged or broken skin

When using this product

- keep out of eyes. Rinse with water to remove.

Stop use and ask a doctor if

- rash occurs

Keep out of reach of children.

If swallowed, get medical help or contact a Poison Control Center right away.

Directions

- apply liberally 15 minutes before sun exposure
- apply to all skin exposed to the sun
- reapply:
- after 80 minutes of swimming or sweating
- immediately after towel drying
- at least every 2 hours
- Sun Protection Measures. Spending time in the sun increases your risk of skin cancer and early skin aging. To decrease this risk, regularly use a sunscreen with a Broad Spectrum SPF value of 15 or higher and other sun protection measures including:
- limit time in the sun, especially from 10 a.m. - 2 p.m.
- wear long-sleeved shirts, pants, hats and sunglasses
- children under 6 months of age: Ask a doctor

Other Information

- Protect the product in this container from excessive heat and direct sun

Inactive ingredients

water, diethylhexyl 2,6-naphthalate, butyloctyl salicylate, styrene/acrylates copolymer, aluminum starch octenylsuccinate, neopentyl glycol diheptanoate, glyceryl stearate, silica, polyester-7, beeswax, acrylates/C10-30 alkyl acrylate crosspolymer, glycerin, potassium hydroxide, chlorphenesin, tocopherol, benzyl alcohol, arachidyl alcohol, fragrance, PEG-100 stearate, behenyl alcohol, arachidyl glucoside, disodium EDTA, amyl cinnamal, sodium ascorbyl phosphate

Questions?

1-800-632-6900

Disclaimers

May stain or damage some fabrics or surfaces

*COPPERTONE® IS A REGISTERED TRADEMARK OF BEIERSDORF AG. BEIERSDIRF AG IS NOT AFFILIATED WITH THE KROGER CO. OR THIS PRODUCT.

Adverse Reactions

DISTRIBUTED BY THE KROGER CO. CINCINNATI, OHIO 45202

QUALITY GUARANTEE

800-632-6900

www.kroger.com

Principal Panel Display

compare to COPPERTONE® COMPLETE LOTION SPF 50

*see back panel

Kroger®

SUNSCREEN lotion

BROAD SPECTRUM SPF 50

UVA/UVB sunscreen

hypoallergenic

water resistant (80 minutes)

SPF 50

8 FL OZ (236 mL)